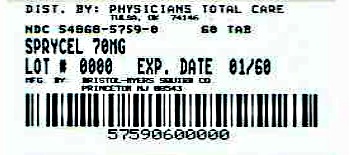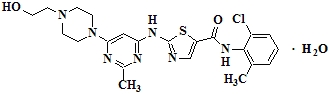 DRUG LABEL: SPRYCEL
                        
NDC: 54868-5759 | Form: TABLET
Manufacturer: Physicians Total Care, Inc.
Category: prescription | Type: HUMAN PRESCRIPTION DRUG LABEL
Date: 20120601

ACTIVE INGREDIENTS: dasatinib 70 mg/1 1
INACTIVE INGREDIENTS: croscarmellose sodium; hydroxypropyl cellulose; hypromelloses; polyethylene glycols; lactose monohydrate; cellulose, microcrystalline; hydroxypropyl cellulose; magnesium stearate; titanium dioxide

HIGHLIGHTS OF PRESCRIBING INFORMATION

These highlights do not include all the information needed to use SPRYCEL safely and effectively. See full prescribing information for SPRYCEL.
SPRYCEL® (dasatinib) Tablet for Oral Use
Initial U.S. Approval: 2006

RECENT MAJOR CHANGES

Warnings and Precautions,
Pulmonary Arterial Hypertension (5.6) 10/2011

1 INDICATIONS AND USAGE

SPRYCEL is a kinase inhibitor indicated for the treatment of

- newly diagnosed adults with Philadelphia chromosome-positive (Ph+) chronic myeloid leukemia (CML) in chronic phase. The trial is ongoing and further data will be required to determine long-term outcome. (1, 14)
- adults with chronic, accelerated, or myeloid or lymphoid blast phase Ph+ CML with resistance or intolerance to prior therapy including imatinib. (1, 14)
- adults with Philadelphia chromosome-positive acute lymphoblastic leukemia (Ph+ ALL) with resistance or intolerance to prior therapy. (1, 14)

2 DOSAGE AND ADMINISTRATION

- Chronic phase CML: 100 mg once daily. (2)
- Accelerated phase CML, myeloid or lymphoid blast phase CML, or Ph+ ALL: 140 mg once daily. (2)

Administered orally, with or without a meal. Tablets should not be crushed or cut. (2)

3 DOSAGE FORMS AND STRENGTHS

Tablets: 20 mg, 50 mg, 70 mg, 80 mg, 100 mg, and 140 mg. (3, 16)

4 CONTRAINDICATIONS

None. (4)

5 WARNINGS AND PRECAUTIONS

- Myelosuppression: Severe thrombocytopenia, neutropenia, and anemia may occur and require dose interruption or reduction. Monitor complete blood counts regularly. (2.3, 5.1, 6.1)
- Bleeding Related Events (mostly associated with severe thrombocytopenia): CNS and gastrointestinal hemorrhages, including fatalities, have occurred. Severe hemorrhage may require treatment interruptions and transfusions. Use SPRYCEL with caution in patients requiring medications that inhibit platelet function or anticoagulants. (5.2, 6.1)
- Fluid Retention: SPRYCEL is associated with fluid retention, sometimes severe, including ascites, edema, and pleural and pericardial effusions. Manage with appropriate supportive care measures. (5.3, 6.1)
- QT Prolongation: Use SPRYCEL with caution in patients who have or may develop prolongation of the QT interval. (5.4)
- Congestive Heart Failure, Left Ventricular Dysfunction and Myocardial Infarction: Monitor patients for signs and symptoms consistent with cardiac dysfunction and treat appropriately. (5.5, 6.1)
- Pulmonary Arterial Hypertension (PAH): SPRYCEL may increase the risk of developing PAH which may be reversible on discontinuation. Evaluate patients for signs and symptoms of underlying cardiopulmonary disease prior to initiating SPRYCEL and during treatment. (5.6)
- Use in Pregnancy: Fetal harm may occur when administered to a pregnant woman. Women should be advised of the potential hazard to the fetus and to avoid becoming pregnant. (5.7, 8.1)

6 ADVERSE REACTIONS

Most common adverse reactions (≥10%) in patients with newly diagnosed chronic phase CML included myelosuppression, fluid retention, diarrhea, headache, musculoskeletal pain, and rash. Most common adverse reactions (≥20%) in patients with resistance or intolerance to prior imatinib therapy included myelosuppression, fluid retention events, diarrhea, headache, dyspnea, skin rash, fatigue, nausea, and hemorrhage. (6.1)

To report SUSPECTED ADVERSE REACTIONS, contact Bristol-Myers Squibb at 1-800-721-5072 or FDA at 1-800-FDA-1088 or www.fda.gov/medwatch

7 DRUG INTERACTIONS

- CYP3A4 Inhibitors: May increase dasatinib drug levels and should be avoided. If coadministration cannot be avoided, monitor closely and consider reducing SPRYCEL dose. (2.1, 7.1)
- CYP3A4 Inducers: May decrease dasatinib drug levels. If coadministration cannot be avoided, consider increasing SPRYCEL dose. (2.1, 7.2)
- Antacids: May decrease dasatinib drug levels. Avoid simultaneous administration. If needed, administer the antacid at least 2 hours prior to or 2 hours after the dose of SPRYCEL. (7.2)
- H2 Antagonists/Proton Pump Inhibitors: May decrease dasatinib drug levels. Consider antacids in place of H2 antagonists or proton pump inhibitors. (7.2)

8 USE IN SPECIFIC POPULATIONS

- Hepatic Impairment: Use SPRYCEL with caution in patients with hepatic impairment. (8.6)

FULL PRESCRIBING INFORMATION

1 INDICATIONS AND USAGE

SPRYCEL® (dasatinib) is indicated for the treatment of adults with

- newly diagnosed Philadelphia chromosome-positive (Ph+) chronic myeloid leukemia (CML) in chronic phase. The effectiveness of SPRYCEL is based on cytogenetic response and major molecular response rates [see Clinical Studies (14.1)]. The trial is ongoing and further data will be required to determine long-term outcome.
- chronic, accelerated, or myeloid or lymphoid blast phase Ph+ CML with resistance or intolerance to prior therapy including imatinib.
- Philadelphia chromosome-positive acute lymphoblastic leukemia (Ph+ ALL) with resistance or intolerance to prior therapy.

2 DOSAGE AND ADMINISTRATION

The recommended starting dosage of SPRYCEL for chronic phase CML is 100 mg administered orally once daily. The recommended starting dosage of SPRYCEL for accelerated phase CML, myeloid or lymphoid blast phase CML, or Ph+ ALL is 140 mg administered orally once daily. Tablets should not be crushed or cut; they should be swallowed whole. SPRYCEL can be taken with or without a meal, either in the morning or in the evening.

In clinical studies, treatment with SPRYCEL was continued until disease progression or until no longer tolerated by the patient. The effect of stopping treatment after the achievement of a complete cytogenetic response (CCyR) has not been investigated.

2.1 Dose Modification

Concomitant Strong CYP3A4 inducers: The use of concomitant strong CYP3A4 inducers may decrease dasatinib plasma concentrations and should be avoided (eg, dexamethasone, phenytoin, carbamazepine, rifampin, rifabutin, phenobarbital). St. John’s Wort may decrease dasatinib plasma concentrations unpredictably and should be avoided. If patients must be coadministered a strong CYP3A4 inducer, based on pharmacokinetic studies, a SPRYCEL dose increase should be considered. If the dose of SPRYCEL is increased, the patient should be monitored carefully for toxicity [see Drug Interactions (7.2)].

Concomitant Strong CYP3A4 inhibitors: CYP3A4 inhibitors (eg, ketoconazole, itraconazole, clarithromycin, atazanavir, indinavir, nefazodone, nelfinavir, ritonavir, saquinavir, telithromycin, and voriconazole) may increase dasatinib plasma concentrations. Grapefruit juice may also increase plasma concentrations of dasatinib and should be avoided.

Selection of an alternate concomitant medication with no or minimal enzyme inhibition potential, if possible, is recommended. If SPRYCEL must be administered with a strong CYP3A4 inhibitor, a dose decrease should be considered. Based on pharmacokinetic studies, a dose decrease to 20 mg daily should be considered for patients taking SPRYCEL 100 mg daily. For patients taking SPRYCEL 140 mg daily, a dose decrease to 40 mg daily should be considered. These reduced doses of SPRYCEL are predicted to adjust the area under the curve (AUC) to the range observed without CYP3A4 inhibitors. However, there are no clinical data with these dose adjustments in patients receiving strong CYP3A4 inhibitors. If SPRYCEL is not tolerated after dose reduction, either the strong CYP3A4 inhibitor must be discontinued, or SPRYCEL should be stopped until treatment with the inhibitor has ceased. When the strong inhibitor is discontinued, a washout period of approximately 1 week should be allowed before the SPRYCEL dose is increased. [See Drug Interactions (7.1).]

2.2 Dose Escalation

In clinical studies of adult CML and Ph+ ALL patients, dose escalation to 140 mg once daily (chronic phase CML) or 180 mg once daily (advanced phase CML and Ph+ ALL) was allowed in patients who did not achieve a hematologic or cytogenetic response at the recommended starting dosage.

2.3 Dose Adjustment for Adverse Reactions

Myelosuppression

In clinical studies, myelosuppression was managed by dose interruption, dose reduction, or discontinuation of study therapy. Hematopoietic growth factor has been used in patients with resistant myelosuppression. Guidelines for dose modifications are summarized in Table 1.

Table 1: Dose Adjustments for Neutropenia and Thrombocytopenia
Chronic Phase CML (starting dose 100 mg once daily) | ANC* <0.5 × 10^9/L or Platelets <50 × 10^9/L | 1. Stop SPRYCEL until ANC ≥1.0 × 10^9/L and platelets ≥50 × 10^9/L.
Chronic Phase CML (starting dose 100 mg once daily) | ANC* <0.5 × 10^9/L or Platelets <50 × 10^9/L | 2. Resume treatment with SPRYCEL at the original starting dose if recovery occurs in ≤7 days.
Chronic Phase CML (starting dose 100 mg once daily) | ANC* <0.5 × 10^9/L or Platelets <50 × 10^9/L | 3. If platelets <25 × 10^9/L or recurrence of ANC <0.5 × 10^9/L for >7 days, repeat Step 1 and resume SPRYCEL at a reduced dose of 80 mg once daily for second episode. For third episode, further reduce dose to 50 mg once daily (for newly diagnosed patients) or discontinue SPRYCEL (for patients resistant or intolerant to prior therapy including imatinib).
Accelerated Phase CML, Blast Phase CML and Ph+ ALL (starting dose 140 mg once daily) | ANC* <0.5 × 10^9/L or Platelets <10 × 10^9/L | 1. Check if cytopenia is related to leukemia (marrow aspirate or biopsy).
Accelerated Phase CML, Blast Phase CML and Ph+ ALL (starting dose 140 mg once daily) | ANC* <0.5 × 10^9/L or Platelets <10 × 10^9/L | 2. If cytopenia is unrelated to leukemia, stop SPRYCEL until ANC ≥1.0 × 10^9/L and platelets ≥20 × 10^9/L and resume at the original starting dose.
Accelerated Phase CML, Blast Phase CML and Ph+ ALL (starting dose 140 mg once daily) | ANC* <0.5 × 10^9/L or Platelets <10 × 10^9/L | 3. If recurrence of cytopenia, repeat Step 1 and resume SPRYCEL at a reduced dose of 100 mg once daily (second episode) or 80 mg once daily (third episode).
Accelerated Phase CML, Blast Phase CML and Ph+ ALL (starting dose 140 mg once daily) | ANC* <0.5 × 10^9/L or Platelets <10 × 10^9/L | 4. If cytopenia is related to leukemia, consider dose escalation to 180 mg once daily.
* ANC: absolute neutrophil count

Non-hematological adverse reactions

If a severe non-hematological adverse reaction develops with SPRYCEL use, treatment must be withheld until the event has resolved or improved. Thereafter, treatment can be resumed as appropriate at a reduced dose depending on the initial severity of the event.

3 DOSAGE FORMS AND STRENGTHS

SPRYCEL (dasatinib) Tablets are available as 20-mg, 50-mg, 70-mg, 80-mg, 100-mg, and 140-mg white to off-white, biconvex, film-coated tablets. [See How Supplied (16.1).]

4 CONTRAINDICATIONS

None.

5 WARNINGS AND PRECAUTIONS

5.1 Myelosuppression

Treatment with SPRYCEL is associated with severe (NCI CTC Grade 3 or 4) thrombocytopenia, neutropenia, and anemia. Their occurrence is more frequent in patients with advanced phase CML or Ph+ ALL than in chronic phase CML. In a dose-optimization study in patients with resistance or intolerance to prior imatinib therapy and chronic phase CML, Grade 3 or 4 myelosuppression was reported less frequently in patients treated with 100 mg once daily than in patients treated with other dosing regimens.

Perform complete blood counts weekly for the first 2 months and then monthly thereafter, or as clinically indicated. Myelosuppression was generally reversible and usually managed by withholding SPRYCEL temporarily or dose reduction [see Dosage and Administration (2.3) and Adverse Reactions (6.1)].

5.2 Bleeding Related Events

In addition to causing thrombocytopenia in human subjects, dasatinib caused platelet dysfunction in vitro. In all clinical studies, severe central nervous system (CNS) hemorrhages, including fatalities, occurred in 1% of patients receiving SPRYCEL. Severe gastrointestinal hemorrhage, including fatalities, occurred in 4% of patients and generally required treatment interruptions and transfusions. Other cases of severe hemorrhage occurred in 2% of patients. Most bleeding events were associated with severe thrombocytopenia.

Patients were excluded from participation in initial SPRYCEL clinical studies if they took medications that inhibit platelet function or anticoagulants. In subsequent trials, the use of anticoagulants, aspirin, and non-steroidal anti-inflammatory drugs (NSAIDs) was allowed concurrently with SPRYCEL if the platelet count was >50,000–75,000 per microliter. Exercise caution if patients are required to take medications that inhibit platelet function or anticoagulants.

5.3 Fluid Retention

SPRYCEL is associated with fluid retention. In clinical trials, severe fluid retention was reported in up to 10% of patients. Ascites and generalized edema were each reported in <1% of patients. Severe pulmonary edema was reported in 1% of patients. Patients who develop symptoms suggestive of pleural effusion, such as dyspnea or dry cough, should be evaluated by chest X-ray. Severe pleural effusion may require thoracentesis and oxygen therapy. Fluid retention events were typically managed by supportive care measures that include diuretics or short courses of steroids. In dose-optimization studies, fluid retention events were reported less frequently with once daily dosing than with other dosing regimens.

5.4 QT Prolongation

In vitro data suggest that dasatinib has the potential to prolong cardiac ventricular repolarization (QT interval). Of the 2440 patients with CML treated with SPRYCEL in clinical studies, 15 patients (<1%) had QTc prolongation reported as an adverse reaction. Twenty-two patients (1%) experienced a QTcF >500 ms. In 865 patients with leukemia treated with SPRYCEL in five Phase 2 single-arm studies, the maximum mean changes in QTcF (90% upper bound CI) from baseline ranged from 7.0 ms to 13.4 ms.

Administer SPRYCEL with caution to patients who have or may develop prolongation of QTc. These include patients with hypokalemia or hypomagnesemia, patients with congenital long QT syndrome, patients taking anti-arrhythmic medicines or other medicinal products that lead to QT prolongation, and cumulative high-dose anthracycline therapy. Correct hypokalemia or hypomagnesemia prior to SPRYCEL administration.

5.5 Congestive Heart Failure, Left Ventricular Dysfunction, and Myocardial Infarction

Cardiac adverse reactions were reported in 5.8% of 258 patients taking SPRYCEL, including 1.6% of patients with cardiomyopathy, heart failure congestive, diastolic dysfunction, fatal myocardial infarction, and left ventricular dysfunction. Monitor patients for signs or symptoms consistent with cardiac dysfunction and treat appropriately.

5.6 Pulmonary Arterial Hypertension

SPRYCEL may increase the risk of developing pulmonary arterial hypertension (PAH) which may occur anytime after initiation, including after more than one year of treatment. Manifestations include dyspnea, fatigue, hypoxia, and fluid retention. PAH may be reversible on discontinuation of SPRYCEL. Evaluate patients for signs and symptoms of underlying cardiopulmonary disease prior to initiating SPRYCEL and during treatment. If PAH is confirmed, SPRYCEL should be permanently discontinued.

5.7 Use in Pregnancy

SPRYCEL may cause fetal harm when administered to a pregnant woman. In nonclinical studies, at plasma concentrations below those observed in humans receiving therapeutic doses of dasatinib, embryo-fetal toxicities, including skeletal malformations, were observed in rats and rabbits. There are no adequate and well-controlled studies of SPRYCEL in pregnant women. Women of childbearing potential should be advised to avoid becoming pregnant while receiving treatment with SPRYCEL [see Use in Specific Populations (8.1)].

6 ADVERSE REACTIONS

The following adverse reactions are discussed in greater detail in other sections of the labeling:

- Myelosuppression [see Dosage and Administration (2.3) and Warnings and Precautions (5.1)].
- Bleeding related events [see Warnings and Precautions (5.2)].
- Fluid retention [see Warnings and Precautions (5.3)].
- QT prolongation [see Warnings and Precautions (5.4)].
- Congestive heart failure, left ventricular dysfunction, and myocardial infarction [see Warnings and Precautions (5.5)].
- Pulmonary Arterial Hypertension [see Warnings and Precautions (5.6)].

Because clinical trials are conducted under widely varying conditions, adverse reaction rates observed in the clinical trials of a drug cannot be directly compared to rates in the clinical trials of another drug and may not reflect the rates observed in practice.

The data described below reflect exposure to SPRYCEL in clinical studies including 258 patients with newly diagnosed chronic phase CML and in 2182 patients with imatinib resistant or intolerant CML or Ph+ ALL.

In the newly diagnosed chronic phase CML trial, the median duration of therapy was 18 months; the median average daily dose was 99 mg.

In the imatinib resistant or intolerant CML or Ph+ ALL clinical trials, patients had a minimum of 2 years follow-up (starting dosage 100 mg once daily, 140 mg once daily, 50 mg twice daily, or 70 mg twice daily). Among patients with chronic phase CML and resistance or intolerance to prior imatinib therapy, the median duration of treatment with SPRYCEL 100 mg once daily was 24 months (range 1–33 months). The median duration of treatment with SPRYCEL 140 mg once daily was 15 months (range 0.03–36 months) for accelerated phase CML, 3 months (range 0.03–29 months) for myeloid blast phase CML, and 3 months (range 0.1–10 months) for lymphoid blast CML.

The majority of SPRYCEL-treated patients experienced adverse reactions at some time. In the newly diagnosed chronic phase CML trial, drug was discontinued for adverse reactions in 6% of SPRYCEL-treated patients. Among patients with resistance or intolerance to prior imatinib therapy, the rates of discontinuation for adverse reaction were 15% in chronic phase CML, 16% in accelerated phase CML, 15% in myeloid blast phase CML, 8% in lymphoid blast phase CML, and 8% in Ph+ ALL. In a dose-optimization study in patients with resistance or intolerance to prior imatinib therapy and chronic phase CML, the rate of discontinuation for adverse reaction was lower in patients treated with 100 mg once daily than in patients treated with other dosing regimens (10% and 16%, respectively).

The most frequently reported adverse reactions reported in ≥10% of patients in newly diagnosed chronic phase CML included myelosuppression, fluid retention events (pleural effusion, superficial localized edema, generalized edema), diarrhea, headache, musculoskeletal pain, and rash. Pleural effusions were reported in 31 patients (see Table 2).

The most frequently reported adverse reactions reported in ≥20% of patients with resistance or intolerance to prior imatinib therapy included myelosuppression, fluid retention events, diarrhea, headache, dyspnea, skin rash, fatigue, nausea, and hemorrhage.

The most frequently reported serious adverse reactions in patients with newly diagnosed chronic phase CML included pleural effusion (2%), hemorrhage (2%), congestive heart failure (1%), and pyrexia (1%). The most frequently reported serious adverse reactions in patients with resistance or intolerance to prior imatinib therapy included pleural effusion (11%), gastrointestinal bleeding (4%), febrile neutropenia (4%), dyspnea (3%), pneumonia (3%), pyrexia (3%), diarrhea (3%), infection (2%), congestive heart failure/cardiac dysfunction (2%), pericardial effusion (1%), and CNS hemorrhage (1%).

6.1 Chronic Myeloid Leukemia (CML)

Adverse reactions (excluding laboratory abnormalities) that were reported in at least 10% of patients are shown in Table 2 for newly diagnosed patients with chronic phase CML and Table 3 for CML patients with resistance or intolerance to prior imatinib therapy.

Table 2: Adverse Reactions Reported in ≥10% of Patients with Newly Diagnosed Chronic Phase CML
 | All Grades |  | Grade 3/4
 | SPRYCEL (n=258) | Imatinib (n=258) | SPRYCEL (n=258) | Imatinib (n=258)
Preferred Term | Percent (%) of Patients
Fluid retention | 23 | 43 | 1 | 1
Pleural effusion | 12 | 0 | <1 | 0
Superficial localized edema | 10 | 36 | 0 | <1
Generalized edema | 3 | 7 | 0 | 0
Congestive heart failure/ cardiac dysfunctiona | 2 | 1 | <1 | <1
Pericardial effusion | 2 | <1 | <1 | 0
Pulmonary hypertension | 1 | 0 | 0 | 0
Pulmonary edema | <1 | 0 | 0 | 0
Diarrhea | 18 | 19 | <1 | 1
Headache | 12 | 10 | 0 | 0
Musculoskeletal pain | 12 | 16 | 0 | <1
Rashb | 11 | 17 | 0 | 1
Nausea | 9 | 21 | 0 | 0
Fatigue | 8 | 11 | <1 | 0
Myalgia | 6 | 12 | 0 | 0
Hemorrhagec | 6 | 5 | 1 | 1
Gastrointestinal bleeding | 2 | <1 | 1 | 0
Other bleedingd | 5 | 5 | 0 | 1
CNS bleeding | 0 | <1 | 0 | <1
Vomiting | 5 | 10 | 0 | 0
Muscle inflammation | 4 | 19 | 0 | <1
a Includes cardiac failure acute, cardiac failure congestive, cardiomyopathy, diastolic dysfunction, ejection fraction decreased, and left ventricular dysfunction.
b Includes erythema, erythema multiforme, rash, rash generalized, rash macular, rash papular, rash pustular, skin exfoliation, and rash vesicular.
c Adverse reaction of special interest with <10% frequency.
d Includes conjunctival hemorrhage, ear hemorrhage, ecchymosis, epistaxis, eye hemorrhage, gingival bleeding, hematoma, hematuria, hemoptysis, intra-abdominal hematoma, petechiae, scleral hemorrhage, uterine hemorrhage, and vaginal hemorrhage.

Table 3: Adverse Reactions Reported in ≥10% of Patients with CML Resistant or Intolerant to Prior Imatinib Therapy
 | 100 mg Once Daily |  | 140 mg Once Daily
 | Chronic (n=165) |  | Accelerated (n=157) |  | Myeloid Blast (n=74) |  | Lymphoid Blast (n=33)
Preferred Term | All Grades | Grade 3/4 | All Grades | Grade 3/4 | All Grades | Grade 3/4 | All Grades | Grade 3/4
Preferred Term | Percent (%) of Patients
Fluid Retention | 34 | 4 | 35 | 8 | 34 | 7 | 21 | 6
Superficial localized edema | 18 | 0 | 18 | 1 | 14 | 0 | 3 | 0
Pleural effusion | 18 | 2 | 21 | 7 | 20 | 7 | 21 | 6
Generalized edema | 3 | 0 | 1 | 0 | 3 | 0 | 0 | 0
Pericardial effusion | 2 | 1 | 3 | 1 | 0 | 0 | 0 | 0
Congestive heart failure/ cardiac dysfunctiona | 0 | 0 | 0 | 0 | 4 | 0 | 0 | 0
Pulmonary edema | 0 | 0 | 1 | 0 | 4 | 3 | 0 | 0
Headache | 33 | 1 | 27 | 1 | 18 | 1 | 15 | 3
Diarrhea | 27 | 2 | 31 | 3 | 20 | 5 | 18 | 0
Fatigue | 24 | 2 | 19 | 2 | 20 | 1 | 9 | 3
Dyspnea | 20 | 2 | 20 | 3 | 15 | 3 | 3 | 3
Musculoskeletal pain | 19 | 2 | 11 | 0 | 8 | 1 | 0 | 0
Nausea | 18 | 1 | 19 | 1 | 23 | 1 | 21 | 3
Skin rashb | 17 | 2 | 15 | 0 | 16 | 1 | 21 | 0
Myalgia | 13 | 0 | 7 | 1 | 7 | 1 | 3 | 0
Arthralgia | 12 | 1 | 10 | 0 | 5 | 1 | 0 | 0
Infection (including bacterial, viral, fungal, and non-specified) | 12 | 1 | 10 | 6 | 14 | 7 | 9 | 0
Abdominal pain | 12 | 1 | 6 | 0 | 8 | 3 | 3 | 0
Hemorrhage | 11 | 1 | 26 | 8 | 19 | 9 | 24 | 9
Gastrointestinal bleeding | 2 | 1 | 8 | 6 | 9 | 7 | 9 | 3
CNS bleeding | 0 | 0 | 1 | 1 | 0 | 0 | 3 | 3
Vomiting | 7 | 1 | 11 | 1 | 12 | 0 | 15 | 0
Pyrexia | 5 | 1 | 11 | 2 | 18 | 3 | 6 | 0
Febrile neutropenia | 1 | 1 | 4 | 4 | 12 | 12 | 12 | 12
a Includes ventricular dysfunction, cardiac failure, cardiac failure congestive, cardiomyopathy, congestive cardiomyopathy, diastolic dysfunction, ejection fraction decreased, and ventricular failure.
b Includes drug eruption, erythema, erythema multiforme, erythrosis, exfoliative rash, generalized erythema, genital rash, heat rash, milia, rash, rash erythematous, rash follicular, rash generalized, rash macular, rash maculopapular, rash papular, rash pruritic, rash pustular, skin exfoliation, skin irritation, urticaria vesiculosa, and rash vesicular.

Laboratory Abnormalities

Myelosuppression was commonly reported in all patient populations. The frequency of Grade 3 or 4 neutropenia, thrombocytopenia, and anemia was higher in patients with advanced phase CML than in chronic phase CML (Tables 4 and 5). Myelosuppression was reported in patients with normal baseline laboratory values as well as in patients with pre-existing laboratory abnormalities.

In patients who experienced severe myelosuppression, recovery generally occurred following dose interruption or reduction; permanent discontinuation of treatment occurred in 2% of patients with newly diagnosed chronic phase CML and 5% of patients with resistance or intolerance to prior imatinib therapy [see Warnings and Precautions (5.1)].

Grade 3 or 4 elevations of transaminase or bilirubin and Grade 3 or 4 hypocalcemia, hypokalemia, and hypophosphatemia were reported in patients with all phases of CML but were reported with an increased frequency in patients with myeloid or lymphoid blast phase CML. Elevations in transaminase or bilirubin were usually managed with dose reduction or interruption. Patients developing Grade 3 or 4 hypocalcemia during the course of SPRYCEL therapy often had recovery with oral calcium supplementation.

Laboratory abnormalities reported in patients with newly diagnosed chronic phase CML are shown in Table 4. There were no discontinuations of SPRYCEL therapy in this patient population due to biochemical laboratory parameters.

Table 4: CTC Grade 3/4 Laboratory Abnormalities in Patients with Newly Diagnosed Chronic Phase CML
 | SPRYCEL (n=258) | Imatinib (n=258)
 | Percent (%) of Patients
Hematology Parameters
Neutropenia | 22 | 20
Thrombocytopenia | 19 | 10
Anemia | 11 | 7
Biochemistry Parameters
Hypophosphatemia | 5 | 24
Hypokalemia | 0 | 2
Hypocalcemia | 3 | 2
Elevated SGPT (ALT) | <1 | 1
Elevated SGOT (AST) | <1 | 1
Elevated Bilirubin | 1 | 0
Elevated Creatinine | <1 | 1
CTC grades: neutropenia (Grade 3 ≥0.5–<1.0 × 10^9/L, Grade 4 <0.5 × 10^9/L); thrombocytopenia (Grade 3 ≥25–<50 × 10^9/L, Grade 4 <25 × 10^9/L); anemia (hemoglobin Grade 3 ≥65–<80 g/L, Grade 4 <65 g/L); elevated creatinine (Grade 3 >3–6 × upper limit of normal range (ULN), Grade 4 >6 × ULN); elevated bilirubin (Grade 3 >3–10 × ULN, Grade 4 >10 × ULN); elevated SGOT or SGPT (Grade 3 >5–20 × ULN, Grade 4 >20 × ULN); hypocalcemia (Grade 3 <7.0–6.0 mg/dL, Grade 4 <6.0 mg/dL); hypophosphatemia (Grade 3 <2.0–1.0 mg/dL, Grade 4 <1.0 mg/dL); hypokalemia (Grade 3 <3.0–2.5 mmol/L, Grade 4 <2.5 mmol/L).

Laboratory abnormalities reported in patients with CML resistant or intolerant to imatinib who received the recommended starting doses of SPRYCEL are shown by disease phase in Table 5.

Table 5: CTC Grade 3/4 Laboratory Abnormalities in Clinical Studies of CML: Resistance or Intolerance to Prior Imatinib Therapy
 |  | Advanced Phase CML
 | Chronic Phase CML | 140 mg Once Daily
 | 100 mg Once Daily (n=165) | Accelerated Phase (n=157) | Myeloid Blast Phase (n=74) | Lymphoid Blast Phase (n=33)
 | Percent (%) of Patients
Hematology Parameters
Neutropenia | 36 | 58 | 77 | 79
Thrombocytopenia | 23 | 63 | 78 | 85
Anemia | 13 | 47 | 74 | 52
Biochemistry Parameters
Hypophosphatemia | 10 | 13 | 12 | 18
Hypokalemia | 2 | 7 | 11 | 15
Hypocalcemia | <1 | 4 | 9 | 12
Elevated SGPT (ALT) | 0 | 2 | 5 | 3
Elevated SGOT (AST) | <1 | 0 | 4 | 3
Elevated Bilirubin | <1 | 1 | 3 | 6
Elevated Creatinine | 0 | 2 | 8 | 0
CTC grades: neutropenia (Grade 3 ≥0.5–<1.0 × 10^9/L, Grade 4 <0.5 × 10^9/L); thrombocytopenia (Grade 3 ≥25–<50 × 10^9/L, Grade 4 <25 × 10^9/L); anemia (hemoglobin Grade 3 ≥65–<80 g/L, Grade 4 <65 g/L); elevated creatinine (Grade 3 >3–6 × upper limit of normal range (ULN), Grade 4 >6 × ULN); elevated bilirubin (Grade 3 >3–10 × ULN, Grade 4 >10 × ULN); elevated SGOT or SGPT (Grade 3 >5–20 × ULN, Grade 4 >20 × ULN); hypocalcemia (Grade 3 <7.0–6.0 mg/dL, Grade 4 <6.0 mg/dL); hypophosphatemia (Grade 3 <2.0–1.0 mg/dL, Grade 4 <1.0 mg/dL); hypokalemia (Grade 3 <3.0–2.5 mmol/L, Grade 4 <2.5 mmol/L).

6.2 Philadelphia Chromosome-Positive Acute Lymphoblastic Leukemia (Ph+ ALL)

A total of 135 patients with Ph+ ALL were treated with SPRYCEL in clinical studies. The median duration of treatment was 3 months (range 0.03–31 months). The safety profile of patients with Ph+ ALL was similar to those with lymphoid blast phase CML. The most frequently reported adverse reactions included fluid retention events, such as pleural effusion (24%) and superficial edema (19%), and gastrointestinal disorders, such as diarrhea (31%), nausea (24%), and vomiting (16%). Hemorrhage (19%), pyrexia (17%), rash (16%), and dyspnea (16%) were also frequently reported. The most frequently reported serious adverse reactions included pleural effusion (11%), gastrointestinal bleeding (7%), febrile neutropenia (6%), infection (5%), pyrexia (4%), pneumonia (3%), diarrhea (3%), nausea (2%), vomiting (2%), and colitis (2%).

6.3 Additional Data From Clinical Trials

The following adverse reactions were reported in patients in the SPRYCEL clinical studies at a frequency of 1%–<10%, 0.1%–<1%, or <0.1%. These events are included on the basis of clinical relevance.

Gastrointestinal Disorders: 1%–<10% – mucosal inflammation (including mucositis/stomatitis), dyspepsia, abdominal distension, constipation, gastritis, colitis (including neutropenic colitis), oral soft tissue disorder; 0.1%–<1% – ascites, dysphagia, anal fissure, upper gastrointestinal ulcer, esophagitis, pancreatitis; <0.1% – protein losing gastroenteropathy.

General Disorders and Administration Site Conditions: 1%–<10% – asthenia, pain, chest pain, chills; 0.1%–<1% – malaise, temperature intolerance.

Skin and Subcutaneous Tissue Disorders: 1%–<10% – pruritus, alopecia, acne, dry skin, hyperhidrosis, urticaria, dermatitis (including eczema); 0.1%–<1% – pigmentation disorder, skin ulcer, bullous conditions, photosensitivity, nail disorder, acute febrile neutrophilic dermatosis, panniculitis, palmar-plantar erythrodysesthesia syndrome.

Respiratory, Thoracic, and Mediastinal Disorders: 1%–<10% – cough, lung infiltration, pneumonitis, pulmonary hypertension; 0.1%–<1% – asthma, bronchospasm; <0.1% – acute respiratory distress syndrome.

Nervous System Disorders: 1%–<10% – neuropathy (including peripheral neuropathy), dizziness, dysgeusia, somnolence; 0.1%–<1% – amnesia, tremor, syncope; <0.1% – convulsion, cerebrovascular accident, transient ischemic attack, optic neuritis.

Blood and Lymphatic System Disorders: 1%–<10% – pancytopenia; <0.1% – aplasia pure red cell.

Musculoskeletal and Connective Tissue Disorders: 1%–<10% – muscular weakness; 0.1%–<1% – musculoskeletal stiffness, rhabdomyolysis; <0.1% – tendonitis.

Investigations: 1%–<10% – weight increased, weight decreased; 0.1%–<1% – blood creatine phosphokinase increased.

Infections and Infestations: 1%–<10% – pneumonia (including bacterial, viral, and fungal), upper respiratory tract infection/inflammation, herpes virus infection, enterocolitis infection; 0.1%–<1% – sepsis (including fatal outcomes).

Metabolism and Nutrition Disorders: 1%–<10% – anorexia, appetite disturbances; 0.1%–<1% – hyperuricemia, hypoalbuminemia.

Cardiac Disorders: 1%–<10% – arrhythmia (including tachycardia), palpitations; 0.1%–<1% – angina pectoris, cardiomegaly, pericarditis, ventricular arrhythmia (including ventricular tachycardia); <0.1% – cor pulmonale, myocarditis, acute coronary syndrome.

Eye Disorders: 1%–<10% – visual disorder (including visual disturbance, vision blurred, and visual acuity reduced), dry eye; 0.1% –<1% – conjunctivitis.

Vascular Disorders: 1%–<10% – flushing, hypertension; 0.1%–<1% – hypotension, thrombophlebitis; <0.1% – livedo reticularis.

Psychiatric Disorders: 1%–<10% – insomnia, depression; 0.1%–<1% – anxiety, affect lability, confusional state, libido decreased.

Reproductive System and Breast Disorders: 0.1%–<1% – gynecomastia, menstruation irregular.

Injury, Poisoning, and Procedural Complications: 1%–<10% – contusion.

Ear and Labyrinth Disorders: 1%–<10% – tinnitus; 0.1%–<1% – vertigo.

Hepatobiliary Disorders: 0.1%–<1% – cholestasis, cholecystitis, hepatitis.

Renal and Urinary Disorders: 0.1%–<1% – urinary frequency, renal failure, proteinuria.

Neoplasms Benign, Malignant, and Unspecified: 0.1%–<1% – tumor lysis syndrome.

Immune System Disorders: 0.1%–<1% – hypersensitivity (including erythema nodosum).

6.4 Postmarketing Experience

The following additional adverse reactions have been identified during post approval use of SPRYCEL. Because these reactions are reported voluntarily from a population of uncertain size, it is not always possible to reliably estimate their frequency or establish a causal relationship to drug exposure.

Cardiac disorders: atrial fibrillation/atrial flutter

Vascular disorders: thrombosis/embolism (including pulmonary embolism, deep vein thrombosis)

Respiratory, thoracic, and mediastinal disorders: interstitial lung disease, pulmonary arterial hypertension

7 DRUG INTERACTIONS

7.1 Drugs That May Increase Dasatinib Plasma Concentrations

CYP3A4 Inhibitors: Dasatinib is a CYP3A4 substrate. In a study of 18 patients with solid tumors, 20-mg SPRYCEL once daily coadministered with 200 mg of ketoconazole twice daily increased the dasatinib Cmax and AUC by four- and five-fold, respectively. Concomitant use of SPRYCEL and drugs that inhibit CYP3A4 may increase exposure to dasatinib and should be avoided. In patients receiving treatment with SPRYCEL, close monitoring for toxicity and a SPRYCEL dose reduction should be considered if systemic administration of a potent CYP3A4 inhibitor cannot be avoided [see Dosage and Administration (2.1)].

7.2 Drugs That May Decrease Dasatinib Plasma Concentrations

CYP3A4 Inducers: When a single morning dose of SPRYCEL was administered following 8 days of continuous evening administration of 600 mg of rifampin, a potent CYP3A4 inducer, the mean Cmax and AUC of dasatinib were decreased by 81% and 82%, respectively. Alternative agents with less enzyme induction potential should be considered. If SPRYCEL must be administered with a CYP3A4 inducer, a dose increase in SPRYCEL should be considered [see Dosage and Administration (2.1)].

Antacids: Nonclinical data demonstrate that the solubility of dasatinib is pH dependent. In a study of 24 healthy subjects, administration of 30 mL of aluminum hydroxide/magnesium hydroxide 2 hours prior to a single 50-mg dose of SPRYCEL was associated with no relevant change in dasatinib AUC; however, the dasatinib Cmax increased 26%. When 30 mL of aluminum hydroxide/magnesium hydroxide was administered to the same subjects concomitantly with a 50-mg dose of SPRYCEL, a 55% reduction in dasatinib AUC and a 58% reduction in Cmax were observed. Simultaneous administration of SPRYCEL with antacids should be avoided. If antacid therapy is needed, the antacid dose should be administered at least 2 hours prior to or 2 hours after the dose of SPRYCEL.

H2 Antagonists/Proton Pump Inhibitors: Long-term suppression of gastric acid secretion by H2 antagonists or proton pump inhibitors (eg, famotidine and omeprazole) is likely to reduce dasatinib exposure. In a study of 24 healthy subjects, administration of a single 50-mg dose of SPRYCEL 10 hours following famotidine reduced the AUC and Cmax of dasatinib by 61% and 63%, respectively. In a study of 14 healthy subjects, administration of a single 100-mg dose of SPRYCEL 22 hours following a 40-mg omeprazole dose at steady state reduced the AUC and Cmax of dasatinib by 43% and 42%, respectively. The concomitant use of H2 antagonists or proton pump inhibitors with SPRYCEL is not recommended. The use of antacids (at least 2 hours prior to or 2 hours after the dose of SPRYCEL) should be considered in place of H2 antagonists or proton pump inhibitors in patients receiving SPRYCEL therapy.

7.3 Drugs That May Have Their Plasma Concentration Altered By Dasatinib

CYP3A4 Substrates: Single-dose data from a study of 54 healthy subjects indicate that the mean Cmax and AUC of simvastatin, a CYP3A4 substrate, were increased by 37% and 20%, respectively, when simvastatin was administered in combination with a single 100-mg dose of SPRYCEL. Therefore, CYP3A4 substrates known to have a narrow therapeutic index such as alfentanil, astemizole, terfenadine, cisapride, cyclosporine, fentanyl, pimozide, quinidine, sirolimus, tacrolimus, or ergot alkaloids (ergotamine, dihydroergotamine) should be administered with caution in patients receiving SPRYCEL.

8 USE IN SPECIFIC POPULATIONS

8.1 Pregnancy

Pregnancy Category D

SPRYCEL may cause fetal harm when administered to a pregnant woman. There are no adequate and well-controlled studies of SPRYCEL in pregnant women. Women of childbearing potential should be advised of the potential hazard to the fetus and to avoid becoming pregnant. If SPRYCEL is used during pregnancy, or if the patient becomes pregnant while taking SPRYCEL, the patient should be apprised of the potential hazard to the fetus.

In nonclinical studies, at plasma concentrations below those observed in humans receiving therapeutic doses of dasatinib, embryo-fetal toxicities were observed in rats and rabbits. Fetal death was observed in rats. In both rats and rabbits, the lowest doses of dasatinib tested (rat: 2.5 mg/kg/day [15 mg/m^2/day] and rabbit: 0.5 mg/kg/day [6 mg/m^2/day]) resulted in embryo-fetal toxicities. These doses produced maternal AUCs of 105 ng•hr/mL (0.3-fold the human AUC in females at a dose of 70 mg twice daily) and 44 ng•hr/mL (0.1-fold the human AUC) in rats and rabbits, respectively. Embryo-fetal toxicities included skeletal malformations at multiple sites (scapula, humerus, femur, radius, ribs, and clavicle), reduced ossification (sternum; thoracic, lumbar, and sacral vertebrae; forepaw phalanges; pelvis; and hyoid body), edema, and microhepatia.

8.3 Nursing Mothers

It is unknown whether SPRYCEL is excreted in human milk. Because many drugs are excreted in human milk and because of the potential for serious adverse reactions in nursing infants from SPRYCEL, a decision should be made whether to discontinue nursing or to discontinue the drug, taking into account the importance of the drug to the mother.

8.4 Pediatric Use

The safety and efficacy of SPRYCEL in patients less than 18 years of age have not been established.

8.5 Geriatric Use

In the newly diagnosed chronic phase CML study, 25 patients (10%) were 65 years of age and over and 7 patients (3%) were 75 years of age and over. Of the 2182 patients in clinical studies of SPRYCEL with resistance or intolerance to imatinib therapy, 547 (25%) were 65 years of age and over and 105 (5%) were 75 years of age and over. No differences in efficacy were observed between older and younger patients. Compared to patients under age 65 years, patients aged 65 years and older are more likely to experience toxicity.

8.6 Hepatic Impairment

The effect of hepatic impairment on the pharmacokinetics of dasatinib was evaluated in healthy volunteers with normal liver function and patients with moderate (Child-Pugh class B) and severe (Child-Pugh class C) hepatic impairment. Compared to the healthy volunteers with normal hepatic function, the dose normalized pharmacokinetic parameters were decreased in the patients with hepatic impairment.

No dosage adjustment is necessary in patients with hepatic impairment [see Clinical Pharmacology (12.3)]. Caution is recommended when administering SPRYCEL to patients with hepatic impairment.

8.7 Renal Impairment

There are currently no clinical studies with SPRYCEL in patients with impaired renal function. Less than 4% of dasatinib and its metabolites are excreted via the kidney.

10 OVERDOSAGE

Experience with overdose of SPRYCEL in clinical studies is limited to isolated cases. Overdosage of 280 mg per day for 1 week was reported in two patients and both developed severe myelosuppression and bleeding. Since SPRYCEL is associated with severe myelosuppression [see Warnings and Precautions (5.1) and Adverse Reactions (6.1)], patients who ingested more than the recommended dosage should be closely monitored for myelosuppression and given appropriate supportive treatment.

Acute overdose in animals was associated with cardiotoxicity. Evidence of cardiotoxicity included ventricular necrosis and valvular/ventricular/atrial hemorrhage at single doses ≥100 mg/kg (600 mg/m^2) in rodents. There was a tendency for increased systolic and diastolic blood pressure in monkeys at single doses ≥10 mg/kg (120 mg/m^2).

11 DESCRIPTION

SPRYCEL (dasatinib) is a kinase inhibitor. The chemical name for dasatinib is N-(2-chloro-6-methylphenyl)-2-[[6-[4-(2-hydroxyethyl)-1-piperazinyl]-2-methyl-4-pyrimidinyl]amino]-5-thiazolecarboxamide, monohydrate. The molecular formula is C22H26ClN7O2S • H2O, which corresponds to a formula weight of 506.02 (monohydrate). The anhydrous free base has a molecular weight of 488.01. Dasatinib has the following chemical structure:

Dasatinib is a white to off-white powder. The drug substance is insoluble in water and slightly soluble in ethanol and methanol. SPRYCEL tablets are white to off-white, biconvex, film-coated tablets containing dasatinib, with the following inactive ingredients: lactose monohydrate, microcrystalline cellulose, croscarmellose sodium, hydroxypropyl cellulose, and magnesium stearate. The tablet coating consists of hypromellose, titanium dioxide, and polyethylene glycol.

12 CLINICAL PHARMACOLOGY

12.1 Mechanism of Action

Dasatinib, at nanomolar concentrations, inhibits the following kinases: BCR-ABL, SRC family (SRC, LCK, YES, FYN), c-KIT, EPHA2, and PDGFRβ. Based on modeling studies, dasatinib is predicted to bind to multiple conformations of the ABL kinase.

In vitro, dasatinib was active in leukemic cell lines representing variants of imatinib mesylate sensitive and resistant disease. Dasatinib inhibited the growth of chronic myeloid leukemia (CML) and acute lymphoblastic leukemia (ALL) cell lines overexpressing BCR-ABL. Under the conditions of the assays, dasatinib was able to overcome imatinib resistance resulting from BCR-ABL kinase domain mutations, activation of alternate signaling pathways involving the SRC family kinases (LYN, HCK), and multi-drug resistance gene overexpression.

12.3 Pharmacokinetics

Absorption

Maximum plasma concentrations (Cmax) of dasatinib are observed between 0.5 and 6 hours (Tmax) following oral administration. Dasatinib exhibits dose proportional increases in AUC and linear elimination characteristics over the dose range of 15 mg to 240 mg/day. The overall mean terminal half-life of dasatinib is 3–5 hours.

Data from a study of 54 healthy subjects administered a single, 100-mg dose of dasatinib 30 minutes following consumption of a high-fat meal resulted in a 14% increase in the mean AUC of dasatinib. The observed food effects were not clinically relevant.

Distribution

In patients, dasatinib has an apparent volume of distribution of 2505 L, suggesting that the drug is extensively distributed in the extravascular space. Binding of dasatinib and its active metabolite to human plasma proteins in vitro was approximately 96% and 93%, respectively, with no concentration dependence over the range of 100–500 ng/mL.

Metabolism

Dasatinib is extensively metabolized in humans, primarily by the cytochrome P450 enzyme 3A4. CYP3A4 was the primary enzyme responsible for the formation of the active metabolite. Flavin-containing monooxygenase 3 (FMO-3) and uridine diphosphate-glucuronosyltransferase (UGT) enzymes are also involved in the formation of dasatinib metabolites.

The exposure of the active metabolite, which is equipotent to dasatinib, represents approximately 5% of the dasatinib AUC. This indicates that the active metabolite of dasatinib is unlikely to play a major role in the observed pharmacology of the drug. Dasatinib also had several other inactive oxidative metabolites.

Dasatinib is a weak time-dependent inhibitor of CYP3A4. At clinically relevant concentrations, dasatinib does not inhibit CYP1A2, 2A6, 2B6, 2C8, 2C9, 2C19, 2D6, or 2E1. Dasatinib is not an inducer of human CYP enzymes.

Elimination

Elimination is primarily via the feces. Following a single oral dose of [^14C]-labeled dasatinib, approximately 4% and 85% of the administered radioactivity was recovered in the urine and feces, respectively, within 10 days. Unchanged dasatinib accounted for 0.1% and 19% of the administered dose in urine and feces, respectively, with the remainder of the dose being metabolites.

Effects of Age and Gender

Pharmacokinetic analyses of demographic data indicate that there are no clinically relevant effects of age and gender on the pharmacokinetics of dasatinib.

Hepatic Impairment

Dasatinib doses of 50 mg and 20 mg were evaluated in eight patients with moderate (Child-Pugh class B) and seven patients with severe (Child-Pugh class C) hepatic impairment, respectively. Matched controls with normal hepatic function (n=15) were also evaluated and received a dasatinib dose of 70 mg. Compared to subjects with normal liver function, patients with moderate hepatic impairment had decreases in dose normalized Cmax and AUC by 47% and 8%, respectively. Patients with severe hepatic impairment had dose normalized Cmax decreased by 43% and AUC decreased by 28% compared to the normal controls.

These differences in Cmax and AUC are not clinically relevant. Dose adjustment is not necessary in patients with hepatic impairment.

13 NONCLINICAL TOXICOLOGY

13.1 Carcinogenesis, Mutagenesis, Impairment of Fertility

In a two-year carcinogenicity study, rats were administered oral doses of dasatinib at 0.3, 1, and 3 mg/kg/day. The highest dose resulted in a plasma drug exposure (AUC) level equivalent to human exposure at 70 mg twice daily. Dasatinib induced a statistically significant increase in the combined incidence of squamous cell carcinomas and papillomas in the uterus and cervix of high-dose females and prostate adenoma in low-dose males.

Dasatinib was clastogenic when tested in vitro in Chinese hamster ovary cells, with and without metabolic activation. Dasatinib was not mutagenic when tested in an in vitro bacterial cell assay (Ames test) and was not genotoxic in an in vivo rat micronucleus study.

The effects of dasatinib on male and female fertility have not been studied. However, results of repeat-dose toxicity studies in multiple species indicate the potential for dasatinib to impair reproductive function and fertility. Effects evident in male animals included reduced size and secretion of seminal vesicles, and immature prostate, seminal vesicle, and testis. The administration of dasatinib resulted in uterine inflammation and mineralization in monkeys, and cystic ovaries and ovarian hypertrophy in rodents.

14 CLINICAL STUDIES

14.1 Newly Diagnosed Chronic Phase CML

An open-label, multicenter, international, randomized trial was conducted in adult patients with newly diagnosed chronic phase CML. A total of 519 patients were randomized to receive either SPRYCEL 100 mg once daily or imatinib 400 mg once daily. The primary endpoint was the rate of confirmed complete cytogenetic response (CCyR) within 12 months. Confirmed CCyR was defined as a CCyR noted on two consecutive occasions (at least 28 days apart).

Median age was 46 years in the SPRYCEL group and 49 years in the imatinib groups, with 10% and 11% of patients ≥65 years of age. There were slightly more male than female patients in both groups (59% vs 41%). Fifty-three percent of all patients were Caucasian, and 39% were Asian. At baseline, the distribution of Hasford Scores was similar in the SPRYCEL and imatinib treatment groups (low risk: 33% and 34%; intermediate risk: 48% and 47%; high risk: 19% and 19%, respectively).

The median duration of treatment was 14 months for SPRYCEL and 14 months for imatinib. With a minimum of 12 months follow-up, 85% of patients randomized to SPRYCEL and 81% of patients randomized to imatinib were still on study.

Efficacy results are summarized in Table 6.

Table 6: Efficacy Results in Newly Diagnosed Patients with Chronic Phase CML
 | SPRYCEL (n=259) | Imatinib (n=260) | p-value
 | Response rate (95% CI)
Confirmed CCyR within 12 monthsa | 76.8% (71.2–81.8) | 66.2% (60.1–71.9) | p=0.007*
Major Molecular Responseb | 52.1% (45.9–58.3) | 33.8% (28.1–39.9) | p<0.0001*
a Confirmed CCyR is defined as a CCyR noted on two consecutive occasions at least 28 days apart.
b Major molecular response (at any time) was defined as BCR-ABL ratios ≤0.1% by RQ-PCR in peripheral blood samples standardized on the International scale.
*Adjusted for Hasford Score and indicated statistical significance at a pre-defined nominal level of significance.
CI = confidence interval.

Median time to confirmed CCyR was 3.1 months in 199 SPRYCEL responders and 5.6 months in 177 imatinib responders. Median time to MMR was 6.3 months in 135 SPRYCEL responders and 9.2 months in 88 imatinib responders.

Five patients on the dasatinib arm progressed to either accelerated phase or blast crisis while nine patients on the imatinib arm progressed to either accelerated phase or blast crisis.

14.2 Imatinib Resistant or Intolerant CML or Ph+ ALL

The efficacy and safety of SPRYCEL were investigated in adult patients with CML or Ph+ ALL whose disease was resistant to or who were intolerant to imatinib: 1158 patients had chronic phase CML, 858 patients had accelerated phase, myeloid blast phase, or lymphoid blast phase CML, and 130 patients had Ph+ ALL. In a clinical study in chronic phase CML, resistance to imatinib was defined as failure to achieve a complete hematologic response (CHR; after 3 months), major cytogenetic response (MCyR; after 6 months), or complete cytogenetic response (CCyR; after 12 months); or loss of a previous molecular response (with concurrent ≥10% increase in Ph+ metaphases), cytogenetic response, or hematologic response. Imatinib intolerance was defined as inability to tolerate 400 mg or more of imatinib per day or discontinuation of imatinib because of toxicity.

Results described below are based on a minimum of 2 years follow-up after the start of SPRYCEL therapy in patients with a median time from initial diagnosis of approximately 5 years. Across all studies, 48% of patients were women, 81% were white, 15% were black or Asian, 25% were 65 years of age or older, and 5% were 75 years of age or older. Most patients had long disease histories with extensive prior treatment, including imatinib, cytotoxic chemotherapy, interferon, and stem cell transplant. Overall, 80% of patients had imatinib-resistant disease and 20% of patients were intolerant to imatinib. The maximum imatinib dose had been 400–600 mg/day in about 60% of the patients and >600 mg/day in 40% of the patients.

The primary efficacy endpoint in chronic phase CML was MCyR, defined as elimination (CCyR) or substantial diminution (by at least 65%, partial cytogenetic response) of Ph+ hematopoietic cells. The primary efficacy endpoint in accelerated phase, myeloid blast phase, lymphoid blast phase CML, and Ph+ ALL was major hematologic response (MaHR), defined as either a CHR or no evidence of leukemia (NEL).

Chronic Phase CML

Dose-Optimization Study: A randomized, open-label study was conducted in patients with chronic phase CML to evaluate the efficacy and safety of SPRYCEL administered once daily compared with SPRYCEL administered twice daily. Patients with significant cardiac diseases, including myocardial infarction within 6 months, congestive heart failure within 3 months, significant arrhythmias, or QTc prolongation were excluded from the study. The primary efficacy endpoint was MCyR in patients with imatinib-resistant CML. A total of 670 patients, of whom 497 had imatinib-resistant disease, were randomized to the SPRYCEL 100 mg once daily, 140 mg once daily, 50 mg twice daily, or 70 mg twice daily group. Median duration of treatment was 22 months.

Efficacy was achieved across all SPRYCEL treatment groups with the once daily schedule demonstrating comparable efficacy (non-inferiority) to the twice daily schedule on the primary efficacy endpoint (difference in MCyR 1.9%; 95% CI [-6.8%–10.6%]).

Efficacy results are presented in Table 7 for patients with chronic phase CML who received the recommended starting dose of 100 mg once daily. Additional efficacy results in this patient population are described after the table. Results for all patients with chronic phase CML, regardless of dosage (a starting dosage of 100 mg once daily, 140 mg once daily, 50 mg twice daily, or 70 mg twice daily), were consistent with those for patients treated with 100 mg once daily.

Table 7: Efficacy of SPRYCEL in Imatinib Resistant or Intolerant Chronic Phase CML
 | 100 mg Once Daily (n=167)
CHRa% (95% CI) | 92% (86–95)
MCyRb% (95% CI) | 63% (56–71)
CCyR% (95% CI) | 50% (42–58)
a CHR (response confirmed after 4 weeks): WBC ≤ institutional ULN, platelets <450,000/mm^3, no blasts or promyelocytes in peripheral blood, <5% myelocytes plus metamyelocytes in peripheral blood, basophils in peripheral blood <20%, and no extramedullary involvement.
b MCyR combines both complete (0% Ph+ metaphases) and partial (>0%–35%) responses.

In the SPRYCEL 100 mg once daily group, median time to MCyR was 2.9 months (95% CI: [2.8–3.0]). Based on the Kaplan-Meier estimates, 93% (95% CI: [88%–98%]) of patients who had achieved an MCyR maintained that response for 18 months. The estimated rate of progression-free survival and overall survival in all patients treated with 100 mg once daily was 80% (95% CI: [73%–87%]) and 91% (95% CI: [86%–96%]), respectively, at 2 years.

Advanced Phase CML and Ph+ ALL

Dose-Optimization Study: One randomized open-label study was conducted in patients with advanced phase CML (accelerated phase CML, myeloid blast phase CML, or lymphoid blast phase CML) to evaluate the efficacy and safety of SPRYCEL administered once daily compared with SPRYCEL administered twice daily. The primary efficacy endpoint was MaHR. A total of 611 patients were randomized to either the SPRYCEL 140 mg once daily or 70 mg twice daily group. Median duration of treatment was approximately 6 months for both treatment groups. The once daily schedule demonstrated comparable efficacy (non-inferiority) to the twice daily schedule on the primary efficacy endpoint.

The efficacy and safety of SPRYCEL were also investigated in patients with Ph+ ALL in one randomized study (starting dosage 140 mg once daily or 70 mg twice daily) and one single-arm study (starting dosage 70 mg twice daily). The primary efficacy endpoint was MaHR. A total of 130 patients were enrolled in these studies. The median duration of therapy was 3 months.

Response rates are presented in Table 8.

Table 8: Efficacy of SPRYCEL in Imatinib Resistant or Intolerant Advanced Phase CML and Ph+ ALL
 | 140 mg Once Daily
 | Accelerated (n=158) | Myeloid Blast (n=75) | Lymphoid Blast (n=33) | Ph+ ALL (n=40)
MaHRa | 66% | 28% | 42% | 38%
(95% CI) | (59–74) | (18–40) | (26–61) | (23–54)
CHRa | 47% | 17% | 21% | 33%
(95% CI) | (40–56) | (10–28) | (9–39) | (19–49)
NELa | 19% | 11% | 21% | 5%
(95% CI) | (13–26) | (5–20) | (9–39) | (1–17)
MCyRb | 39% | 28% | 52% | 70%
(95% CI) | (31–47) | (18–40) | (34–69) | (54–83)
CCyR | 32% | 17% | 39% | 50%
(95% CI) | (25–40) | (10–28) | (23–58) | (34–66)
a Hematologic response criteria (all responses confirmed after 4 weeks): Major hematologic response: (MaHR) = complete hematologic response (CHR) + no evidence of leukemia (NEL).
CHR: WBC ≤ institutional ULN, ANC ≥1000/mm^3, platelets ≥100,000/mm^3, no blasts or promyelocytes in peripheral blood, bone marrow blasts ≤5%, <5% myelocytes plus metamyelocytes in peripheral blood, basophils in peripheral blood <20%, and no extramedullary involvement.
NEL: same criteria as for CHR but ANC ≥500/mm^3 and <1000/mm^3, or platelets ≥20,000/mm^3 and ≤100,000/mm^3.
b MCyR combines both complete (0% Ph+ metaphases) and partial (>0%–35%) responses.
CI = confidence interval ULN = upper limit of normal range.

In the SPRYCEL 140 mg once daily group, the median time to MaHR was 1.9 months for patients with accelerated phase CML, 1.9 months for patients with myeloid blast phase CML, and 1.8 months for patients with lymphoid blast phase CML.

In patients with myeloid blast phase CML, the median duration of MaHR was 8 months and 9 months for the 140 mg once daily group and the 70 mg twice daily group, respectively. In patients with lymphoid blast phase CML, the median duration of MaHR was 5 months and 8 months for the 140 mg once daily group and the 70 mg twice daily group, respectively. In patients with Ph+ ALL who were treated with SPRYCEL 140 mg once daily, the median duration of MaHR was 4.6 months. The medians of progression-free survival for patients with Ph+ ALL treated with SPRYCEL 140 mg once daily and 70 mg twice daily were 4.0 months and 3.5 months, respectively.

15 REFERENCES

1. NIOSH Alert: Preventing occupational exposures to antineoplastic and other hazardous drugs in healthcare settings. 2004. U.S. Department of Health and Human Services, Public Health Service, Centers for Disease Control and Prevention, National Institute for Occupational Safety and Health, DHHS (NIOSH) Publication No. 2004–165.
2. OSHA Technical Manual, TED 1-0.15A, Section VI: Chapter 2. Controlling Occupational Exposure to Hazardous Drugs. OSHA, 1999, http://www.osha.gov/dts/osta/otm/otm_vi/otm_vi_2.html.
3. American Society of Health-System Pharmacists. ASHP guidelines on handling hazardous drugs. Am J Health-Syst Pharm. (2006) 63:1172–1193.
4. Polovich M, White JM, Kelleher LO (eds). 2005. Chemotherapy and biotherapy guidelines and recommendations for practice (2nd ed). Pittsburgh, PA: Oncology Nursing Society.

16 HOW SUPPLIED/STORAGE AND HANDLING

16.1 How Supplied

SPRYCEL® (dasatinib) tablets are available as described in Table 9.

Table 9: SPRYCEL Trade Presentations
NDC Number | Strength | Description | Tablets per Bottle
54868-5759-0 | 70 mg | white to off-white, biconvex, round, film-coated tablet with “BMS” debossed on one side and “524” on the other side | 60

16.2 Storage

SPRYCEL® tablets should be stored at 20° to 25°C (68° to 77°F); excursions permitted between 15°–30°C (59°–86°F) [see USP Controlled Room Temperature].

16.3 Handling and Disposal

Procedures for proper handling and disposal of anticancer drugs should be considered. Several guidelines on this subject have been published [see References (15)].

SPRYCEL (dasatinib) tablets consist of a core tablet (containing the active drug substance), surrounded by a film coating to prevent exposure of pharmacy and clinical personnel to the active drug substance. However, if tablets are inadvertently crushed or broken, pharmacy and clinical personnel should wear disposable chemotherapy gloves. Personnel who are pregnant should avoid exposure to crushed or broken tablets.

17 PATIENT COUNSELING INFORMATION

See FDA-Approved Patient Labeling.

17.1 Bleeding

Patients should be informed of the possibility of serious bleeding and to report immediately any signs or symptoms suggestive of hemorrhage (unusual bleeding or easy bruising).

17.2 Myelosuppression

Patients should be informed of the possibility of developing low blood cell counts; they should be instructed to report immediately should fever develop, particularly in association with any suggestion of infection.

17.3 Fluid Retention

Patients should be informed of the possibility of developing fluid retention (swelling, weight gain, or shortness of breath) and to seek medical attention if those symptoms arise.

17.4 Pregnancy

Patients should be informed that dasatinib may cause fetal harm when administered to a pregnant woman. Women should be advised of the potential hazard to the fetus and to avoid becoming pregnant. If SPRYCEL is used during pregnancy, or if the patient becomes pregnant while taking SPRYCEL, the patient should be apprised of the potential hazard to the fetus [see Warnings and Precautions (5.7)].

17.5 Gastrointestinal Complaints

Patients should be informed that they may experience nausea, vomiting, or diarrhea with SPRYCEL. If these symptoms are significant, they should seek medical attention.

17.6 Pain

Patients should be informed that they may experience headache or musculoskeletal pain with SPRYCEL. If these symptoms are significant, they should seek medical attention.

17.7 Fatigue

Patients should be informed that they may experience fatigue with SPRYCEL. If this symptom is significant, they should seek medical attention.

17.8 Rash

Patients should be informed that they may experience skin rash with SPRYCEL. If this symptom is significant, they should seek medical attention.

17.9 Lactose

Patients should be informed that SPRYCEL contains 135 mg of lactose monohydrate in a 100-mg daily dose and 189 mg of lactose monohydrate in a 140-mg daily dose.

17.10 Missed Dose

If the patient misses a dose of SPRYCEL, the patient should take the next scheduled dose at its regular time. The patient should not take two doses at the same time.

PATIENT INFORMATION

FDA-Approved Patient Labeling

PATIENT INFORMATION

SPRYCEL® (Spry-sell)

(dasatinib)

Tablets

Read the Patient Information that comes with SPRYCEL before you start taking it and each time you get a refill. There may be new information. This leaflet does not take the place of talking with your healthcare provider about your medical condition or treatment.

What is SPRYCEL?

SPRYCEL® is a prescription medicine used to treat adults who have:

- newly diagnosed Philadelphia chromosome-positive (Ph+) chronic myeloid leukemia (CML) in chronic phase.
- Ph+ CML who no longer benefit from, or did not tolerate, other treatment, including Gleevec® (imatinib mesylate).
- Philadelphia chromosome-positive acute lymphoblastic leukemia (Ph+ ALL) who no longer benefit from, or did not tolerate, other treatment.

It is not known if SPRYCEL is safe and effective in children younger than 18 years old.

What should I tell my healthcare provider before taking SPRYCEL?

Before you take SPRYCEL, tell your healthcare provider if you:

- have problems with your immune system
- have liver problems
- have heart problems
- are lactose intolerant
- have any other medical conditions
- are pregnant or planning to become pregnant. SPRYCEL may harm your unborn baby. Women should not become pregnant while taking SPRYCEL. Talk to your healthcare provider right away if you are pregnant or plan to become pregnant.
- are breastfeeding or plan to breastfeed. It is not known if SPRYCEL passes into your breast milk or if it can harm your baby. You and your healthcare provider should decide if you will take SPRYCEL or breastfeed. You should not do both.

Tell your healthcare provider about all the medicines you take, including prescription and non-prescription medicines, vitamins, antacids, and herbal supplements.

Especially tell your healthcare provider if you take:

- medicines that increase the amount of SPRYCEL in your bloodstream, such as:

 | Nizoral® (ketoconazole), | Nefazodone (serzone, nefadar),
 | Sporanox® (itraconazole), | Invirase® (saquinavir),
 | Norvir® (ritonavir), | Ketek® (telithromycin),
 | Reyataz® (atazanavir sulfate), | E-mycin® (erythromycin),
 | Crixivan® (indinavir), | Biaxin® (clarithromycin).
 | Viracept® (nelfinavir),

- medicines that decrease the amount of SPRYCEL in your bloodstream, such as:

 | Decadron® (dexamethasone), | Rimactane® (rifampin),
 | Dilantin® (phenytoin), | Luminal® (phenobarbital).
 | Tegretol® (carbamazepine),

- medicines whose blood levels might change by taking SPRYCEL, such as:

 | Sandimmune® (cyclosporine), | Rapamune® (sirolimus),
 | Alfenta® (alfentanil), | Prograf® (tacrolimus),
 | Fentanyl® (fentanyl), | Ergomar® (ergotamine).
 | Orap® (pimozide),

SPRYCEL is best absorbed from your stomach into your bloodstream in the presence of stomach acid. You should avoid taking medicines that reduce stomach acid, such as:

 | Tagamet® (cimetidine), | Protonix® (pantoprazole sodium),
 | Pepcid® (famotidine), | Nexium® (esomeprazole),
 | Zantac® (ranitidine), | AcipHex® (rabeprazole),
 | Prilosec® (omeprazole), | Prevacid® (lansoprazole).

Medicines that neutralize stomach acid, such as Maalox® (aluminum hydroxide/magnesium hydroxide), Tums® (calcium carbonate), or Rolaids® (calcium carbonate and magnesia), may be taken up to 2 hours before or 2 hours after SPRYCEL.

Since SPRYCEL therapy may cause bleeding, tell your healthcare provider if you are using blood thinner medicine, such as Coumadin® (warfarin sodium) or aspirin.

Know the medicines you take. Keep a list of your medicines and show it to your healthcare provider and pharmacist when you get a new medicine.

How should I take SPRYCEL?

Take SPRYCEL exactly as prescribed by your healthcare provider.

- Take SPRYCEL with or without food. Try to take SPRYCEL at the same time each day.
- Swallow SPRYCEL tablets whole. Do not break, cut, or crush the tablets.
- You should not drink grapefruit juice while taking SPRYCEL.
- Your healthcare provider may:
  - change your dose of SPRYCEL or
  - tell you to temporarily stop taking SPRYCEL.
- Do not change your dose or stop taking SPRYCEL without first talking with your healthcare provider.
- If you miss a dose of SPRYCEL, take your next scheduled dose at its regular time. Do not take two doses at the same time. Call your healthcare provider or pharmacist if you are not sure what to do.
- If you take too much SPRYCEL, call your healthcare provider or go to the nearest hospital emergency room right away.

What are the possible side effects of SPRYCEL?

SPRYCEL may cause serious side effects, including:

- Low Blood Cell Counts: SPRYCEL may cause low red blood cell counts (anemia), low white blood cell counts (neutropenia), and low platelet counts (thrombocytopenia). Your healthcare provider will do blood tests to check your blood cell counts regularly during your treatment with SPRYCEL. Call your healthcare provider right away if you have a fever or any signs of an infection while taking SPRYCEL.
- Bleeding: SPRYCEL may cause severe bleeding that can lead to death. Call your healthcare provider right away if you have:
  - unusual bleeding or bruising of your skin
  - bright red or dark tar-like stools
  - a decrease in your level of consciousness, headache, or change in speech.
- Your body may hold too much fluid (fluid retention): In severe cases, fluid may build up in the lining of your lungs, the sac around your heart, or your stomach cavity. Call your healthcare provider right away if you get any of these symptoms during treatment with SPRYCEL:
  - swelling all over your body
  - weight gain
  - shortness of breath and cough.
- Heart problems. SPRYCEL may cause an abnormal heart rate, heart problems or a heart attack. It may also cause changes in the blood vessels supplying the lungs. Your healthcare provider will monitor the potassium and magnesium levels in your blood, and your heart function.
- Pulmonary Arterial Hypertension (PAH). SPRYCEL may cause high blood pressure in the vessels of your lungs. PAH may happen at anytime during your treatment with SPRYCEL. Your healthcare provider should check your heart and lungs before and during your treatment with SPRYCEL. Call your healthcare provider right away if you have shortness of breath, tiredness, or swelling all over your body (fluid retention).

Other common side effects of SPRYCEL therapy include:

• diarrhea

• tiredness

• headache

• vomiting

• cough

• muscle pain

• skin rash

• weakness

• fever

• infections

• nausea

Tell your healthcare provider if you have any side effect that bothers you or that does not go away.

These are not all of the possible side effects of SPRYCEL. For more information, ask your healthcare provider or pharmacist.

Call your doctor for medical advice about side effects. You may report side effects to FDA at 1-800-FDA-1088.

How should I store SPRYCEL?

- Store SPRYCEL at room temperature, between 68°F to 77°F (20°C to 25°C).
- Ask your healthcare provider or pharmacist about the right way to throw away outdated or unused SPRYCEL.
- Women who are pregnant should not handle crushed or broken SPRYCEL tablets.
- Keep SPRYCEL and all medicines out of the reach of children and pets.

General information about SPRYCEL

Medicines are sometimes prescribed for purposes other than those listed in the Patient Information leaflet. Do not use SPRYCEL for a condition for which it is not prescribed. Do not give SPRYCEL to other people even if they have the same symptoms you have. It may harm them.

This Patient Information leaflet summarizes the most important information about SPRYCEL. If you would like more information, talk with your healthcare provider. You can ask your healthcare provider or pharmacist for information about SPRYCEL that is written for healthcare professionals.

For more information, go to www.sprycel.com or call 1-800-332-2056.

What are the ingredients in SPRYCEL?

Active ingredient: dasatinib

Inactive ingredients: lactose monohydrate, microcrystalline cellulose, croscarmellose sodium, hydroxypropyl cellulose, and magnesium stearate. The tablet coating consists of hypromellose, titanium dioxide, and polyethylene glycol.

This Patient Package Insert has been approved by the U.S. Food and Drug Administration.

Manufactured by:
Bristol-Myers Squibb Company
Princeton, NJ 08543 USA

Revised: October 2011

Bristol-Myers Squibb Company
Princeton, NJ 08543 USA

1284903A0
Rev October 2011

Additional barcode labeling by:

Physicians Total Care, Inc.

Tulsa, Oklahoma 74146

PRINCIPAL DISPLAY PANEL

NDC 54868-5759-0

60 tablets

SPRYCEL®
(dasatinib)
Tablets
70 mg
Rx only
Do not crush or cut tablet